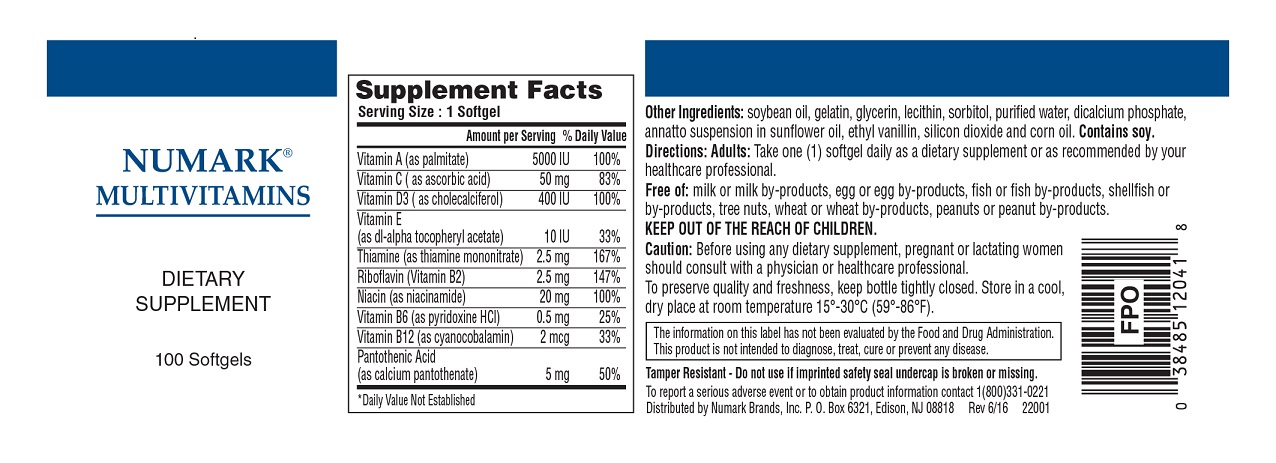 DRUG LABEL: Numark Multivitamins 
NDC: 69846-120 | Form: CAPSULE, LIQUID FILLED
Manufacturer: NUMARK BRANDS, INC
Category: other | Type: DIETARY SUPPLEMENT
Date: 20160819

ACTIVE INGREDIENTS: Vitamin A Palmitate 5000 [iU]/1 1; Ascorbic Acid 50 mg/1 1; Cholecalciferol 400 [iU]/1 1; .alpha.-tocopherol Acetate, Dl- 10 [iU]/1 1; Thiamine Mononitrate 2.5 mg/1 1; Riboflavin 2.5 mg/1 1; Niacinamide 20 mg/1 1; Pyridoxine Hydrochloride 0.5 mg/1 1; Cyanocobalamin 2 ug/1 1; Calcium Pantothenate 5 mg/1 1
INACTIVE INGREDIENTS: Soybean Oil; Gelatin; Glycerin; Lecithin, Soybean; Sorbitol; Water; Calcium Phosphate, Dibasic, Anhydrous; Annatto; Ethyl Vanillin; Silicon Dioxide; Corn Oil

Numark® Multivinamins Dietary Supplement

Supplement Facts

Serving Size : 1 Softgel

 | Amount Per Serving | % Daily Value
Vitamin A (as palmitate) | 5000 IU | 100%
Vitamin C (as ascorbic acid) | 50 mg | 83%
Vitamin D3 (as cholecalciferol) | 400 IU | 100%
Vitamin E (as dl-alpha tocopheryl acetate) | 10 IU | 33%
Thiamine (as thiamine mononitrate) | 2.5 mg | 167%
Riboflavin (Vitamin B2) | 2.5 mg | 147%
Niacin (as niacinamide) | 20 mg | 100%
Vitamin B6 (as pyridoxine HCl) | 0.5 mg | 25%
Vitamin B12 (as cyanocobalamin) | 2 mcg | 33%
Pantothenic Acid (as calcium pantothenate) | 5 mg | 50%
* Daily Value Not Established

Other Ingredients: soybean oil, gelatin, glycerin, lecithin, sorbitol, purified water, dicalcium phosphate, annatto suspension in sunflower oil, ethyl vanillin, silicon dioxide and corn oil. Contains soy.

DOSAGE AND ADMINISTRATION

Directions: Adults: Take one (1) softgel daily as a dietary supplement or as recommended by your healthcare professional.

Free of: Milk or milk by-products, egg or egg by-products, fish or fish by-products, shellfish or by-products, tree nuts, wheat or wheat by-products, peanuts or peanut by-products.

WARNINGS

KEEP OUT OF THE REACH OF CHILDREN.

PRECAUTIONS

Caution: Before using any dietary supplement, pregnant or lactating women should consult with a physician or healthcare professional.

SAFE HANDLING WARNING

To preserve quality and freshness, keep bottle tightly closed. Store in a cool, dry place at room temperature 15º-30ºC (59º-86º)F.

The information on this label has not been evaluated by the Food and Drug Administration.
This product is not intended to diagnose, treat, cure or prevent any disease.

Tamper Resistant - Do not use if imprinted safety seal undercap is broken or missing.

To report a serious adverse event or to obtain product information contact 1(800)331-0221

PACKAGE LABEL.PRINCIPAL DISPLAY PANEL

NUMARK® MULTIVAMINS
DIETARY SUPPLEMENT
100 Softgels
Distributed by Numark Brands, Inc. P.O. Box 6321, Edison, NJ 08818
Rev 6/16
22001